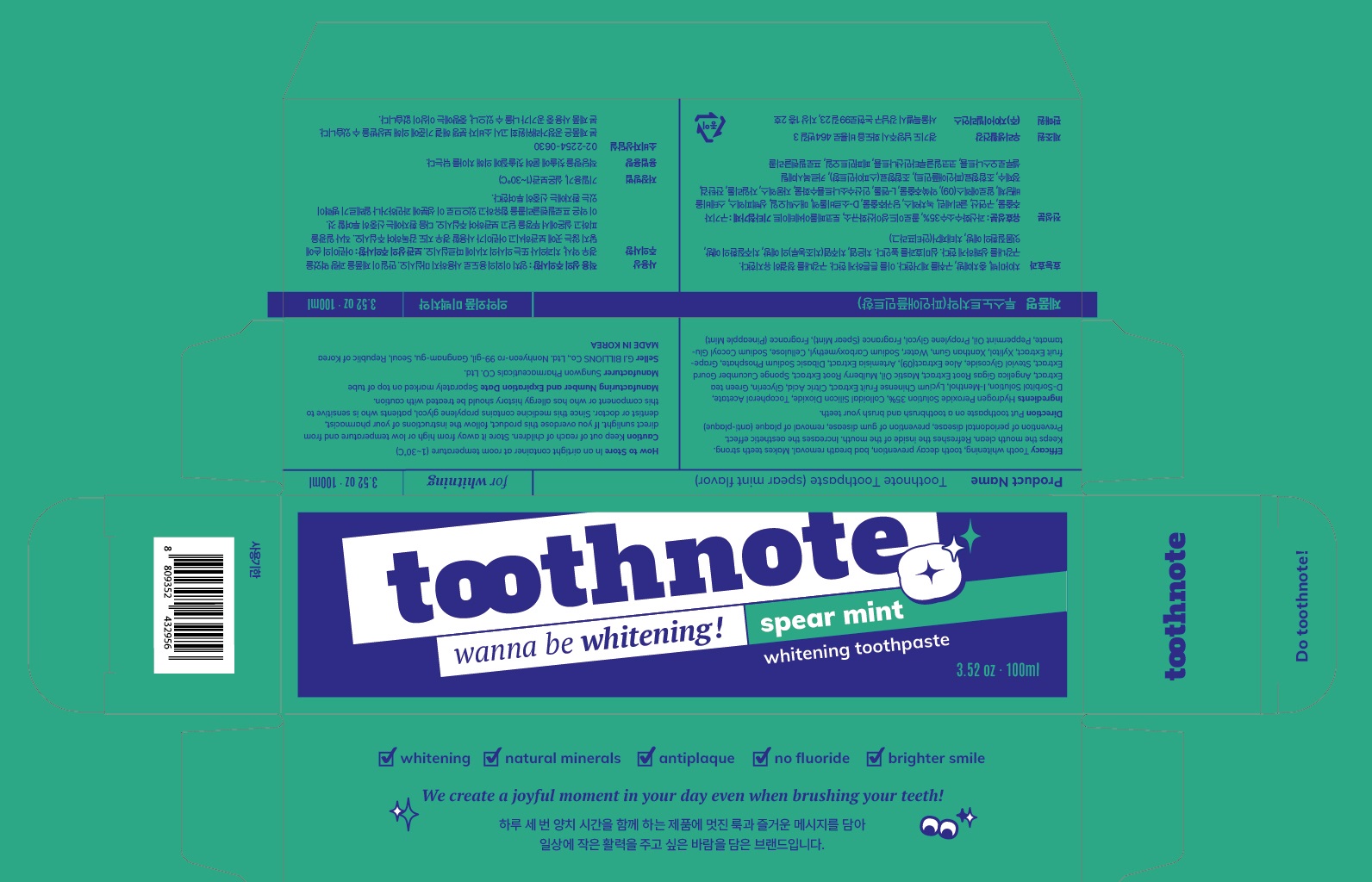 DRUG LABEL: ToothpasteToothpaste (Pineapple mint flavor)
NDC: 73065-0010 | Form: PASTE, DENTIFRICE
Manufacturer: WOORI LIFE & HEALTH
Category: otc | Type: HUMAN OTC DRUG LABEL
Date: 20230502

ACTIVE INGREDIENTS: HYDROGEN PEROXIDE 2.14 g/100 mL; .ALPHA.-TOCOPHEROL ACETATE 0.2 g/100 mL; SILICON DIOXIDE 7 g/100 mL
INACTIVE INGREDIENTS: XYLITOL; WATER

ACTIVE INGREDIENT

Hydrogen peroxide, Tocopheryl acetate, silicon dioxide

PURPOSE

Tooth whitening, tooth decay prevention, bad breath removal. Makes tooth strong.

Keeps the mouth clean, Refreshes the inside of the mouth. lncreases the aesthetic effect. Prevention of periodontal disease, gum disease and, removal of plaque (anti-plaque)

Keep out of reach of children

INDICATIONS AND USAGE

apply appropriate amount of the tooth paste on the tooth brush and brush the teeth

WARNINGS

(1) Do not swallow, gargle fully after using.
(2) If the use of this paste causes gingiva or oral cavity injury, please stop using and consult a doctor or a dentist.
(3) If childern under 6 years of age use, please apply a pea-sized amount each thime. Do not swallow. Please use under the guidance of the guardian.
(4) If children under 6 years of age accidentally ingest large amounts of the paste, please consult a doctor or a dentist immediately.
(5) Keep out of reach of children under 6 years of age.

INACTIVE INGREDIENT

Glycerin

D-Sorbitol solution

Propylene Glycol

Xanthan gum

Carboxymethyl cellulose sodium

Sodium Cocoyl Glutamate

Xylitol

Steviol Glycoside

Green tea extract

Lycium Chinense Fruit Extract

Mulberry Root Extract

Angelica Gigas Root Extract

Graperuit seed extract

Mugwort Extract

Aloe Extract(09)

Mastic oil

Sodium Phosphate

Citric acid

L-Menthol

Spearmint flavor

Peppermint oil

Pineapple mint flavor

Purified water

DOSAGE AND ADMINISTRATION

For dental use only